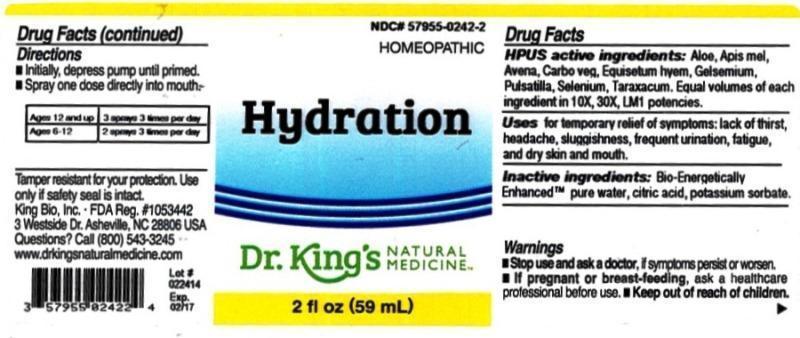 DRUG LABEL: Hydration
NDC: 57955-0242 | Form: LIQUID
Manufacturer: King Bio Inc.
Category: homeopathic | Type: HUMAN OTC DRUG LABEL
Date: 20140310

ACTIVE INGREDIENTS: ALOE 10 [hp_X]/59 mL; APIS MELLIFERA 10 [hp_X]/59 mL; AVENA SATIVA FLOWERING TOP 10 [hp_X]/59 mL; ACTIVATED CHARCOAL 10 [hp_X]/59 mL; EQUISETUM HYEMALE 10 [hp_X]/59 mL; GELSEMIUM SEMPERVIRENS ROOT 10 [hp_X]/59 mL; PULSATILLA VULGARIS 10 [hp_X]/59 mL; SELENIUM 10 [hp_X]/59 mL; TARAXACUM OFFICINALE 10 [hp_X]/59 mL
INACTIVE INGREDIENTS: WATER; CITRIC ACID MONOHYDRATE; POTASSIUM SORBATE

Hydration

ACTIVE INGREDIENT

HPUS active ingredients: Aloe socotrine, Apis mellifica, Avena sativa, Carbo vegetabilis, Equisetum hyemale, Gelsemium sempervirens, Pulsatilla, Selenium metallicum, Taraxacum officinale. Equal volumes of each ingredient in 10X, 30X, LM1 potencies.

PURPOSE

Uses for temporary relief of symptoms: lack of thirst, headache, sluggishness, frequent urination, fatigue, and dry skin and mouth.

Inactive Ingredients:

Bio-Energetically Enhanced™ pure water base, Citric acid and Potassium sorbate.

Warning

- Stop use and ask a doctor. If symptoms persist or worsen.
- If pregnant or breast-feeding, ask a healthcare professional before use.

- Keep out of reach of children

Directions

- Initially, depress pump until primed.
- Spray one dose directly into mouth.
- Ages 12 and up 3 sprays 3 times per day
- Ages 6-12 2 sprays 3 times per day

Other Information: Tamper resistant for your protection. Use only if safety seal is intact.

INDICATIONS AND USAGE

Uses for temporary relief of symptoms:

- lack of thirst
- headache
- sluggishness
- frequent urination
- fatigue and dry skin and mouth